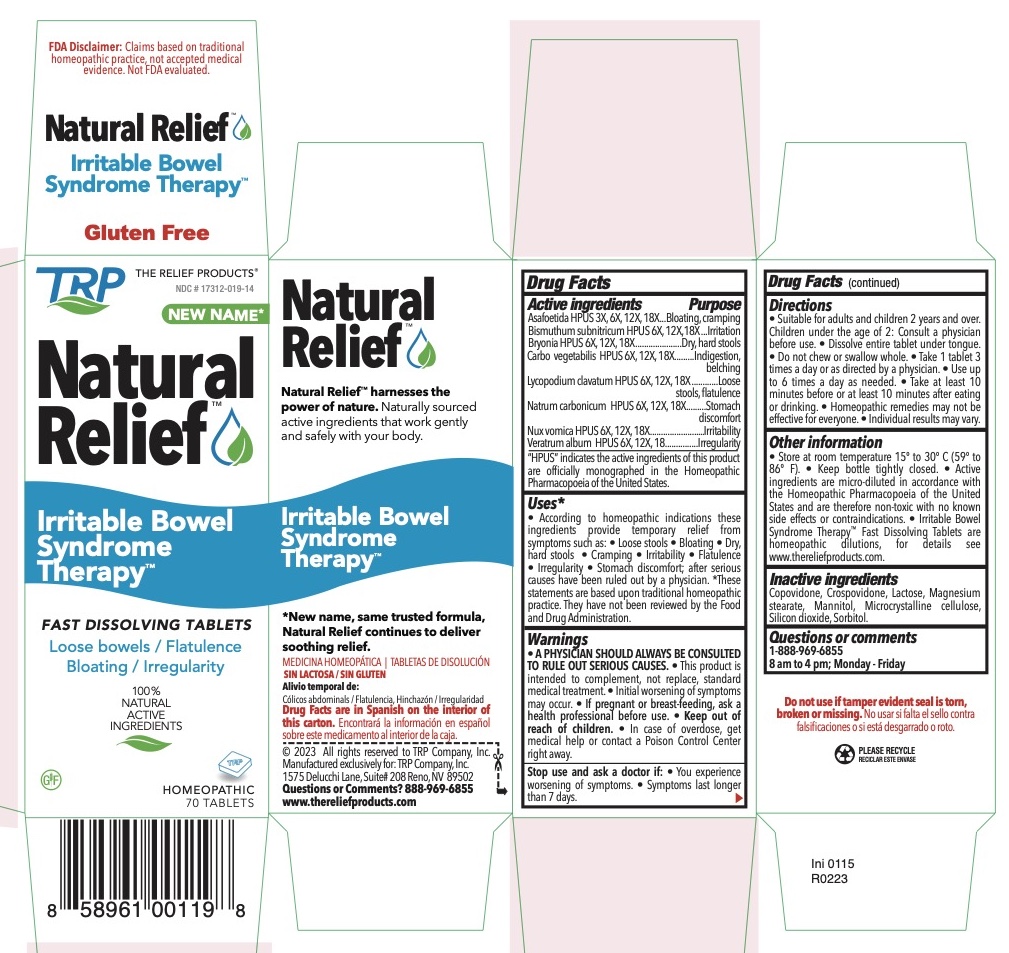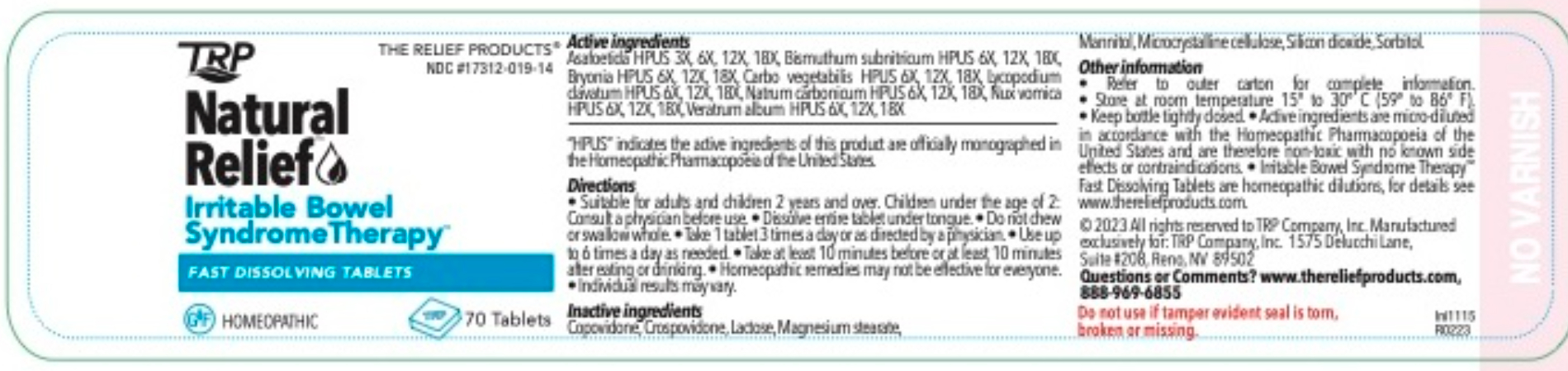 DRUG LABEL: Irritable Bowel Syndrome Therapy
NDC: 17312-019 | Form: TABLET, ORALLY DISINTEGRATING
Manufacturer: TRP Company
Category: homeopathic | Type: HUMAN OTC DRUG LABEL
Date: 20251215

ACTIVE INGREDIENTS: ASAFETIDA 3 [hp_X]/1 1; BISMUTH SUBNITRATE 6 [hp_X]/1 1; BRYONIA ALBA ROOT 6 [hp_X]/1 1; ACTIVATED CHARCOAL 6 [hp_X]/1 1; LYCOPODIUM CLAVATUM SPORE 6 [hp_X]/1 1; SODIUM CARBONATE 6 [hp_X]/1 1; STRYCHNOS NUX-VOMICA SEED 6 [hp_X]/1 1; VERATRUM ALBUM ROOT 6 [hp_X]/1 1
INACTIVE INGREDIENTS: MANNITOL; SORBITOL; CROSPOVIDONE; CELLULOSE, MICROCRYSTALLINE; COPOVIDONE; SILICON DIOXIDE; LACTOSE; MAGNESIUM STEARATE

Irritable Bowel Syndrome Therapy™ Fast Dissolving Tablets

ACTIVE INGREDIENT

Asafoetida HPUS 3x 6x 12x 18x
Bismuthum subnitricum HPUS 6x 12x 18x
Bryonia HPUS 6x 12x 18x
Carbo vegetabilis HPUS 6x 12x 18x
Lycopodium Clavatum HPUS 6x 12x 18x
Natrum carbonicum HPUS 6x 12x 18x
Nux vomica HPUS 6x 12x 18x
Veratrum album HPUS 6x 12x 18x
HPUS indicates the active ingredients are in the Homeopathic Pharmacopoeia of the United States.

PURPOSE

Asafoetida HPUS - Bloating, Cramping

Bismuthum subnitricum HPUS - Irritation

Bryonia HPUS - Dry, hard stools

Carbo vegetabilis HPUS - Indigestion, Belching

Lycopodium Clavatum HPUS - Loose stools, Flatulence

Natrum carbonicum HPUS - Stomach discomfort

Nux vomica HPUS - Irritability

Veratrum album HPUS - Irregularity

PREGNANCY OR BREAST FEEDING

If pregnant or breast-feeding, ask a health professional before use.

Keep out of reach of children

In case of overdose, get medical help or contact a Poison Control Center right away.

Warnings:

USE ONLY AFTER DIAGNOSIS BY A PHYSICIAN AND UNDER THE SUPERVISION OF A PHYSICIAN.

- This product is intended to complement, not replace, standard medical treatment.
- Initial worsening of symptoms may occur.
- A physician should always be consulted to rule out serious causes.

Directions

- Suitable for adults and children 12 years and above.
- Dissolve entire tablet under tongue.
- Do not chew or swallow whole.
- Take 1 tablet 3 times a day or as directed by a physician.
- Use up to 6 times a day as needed.
- Take at least 10 minutes before or at least 10 minutes after eating or drinking.
- Children under the age of 12: consult a physician before use.

Homeopathic remedies may not be effective for everyone.

Other information

- There are no known contraindications.
- Active ingredients are micro-diluted in accordance with the Homeopathic Pharmacopoeia of the United States and are therefore non-toxic with no known side effects.
- Store in a cool dark location.
- Irritable Bowel Syndrome Therapy™ Homeopathic Fast Dissolving Tablet are homeopathic dilutions: see www.thereliefproducts.com for details.

Inactive Ingredients

Advantol® 300, Lactose, Magnesium Stearate, Mannitol, Microcrystalline Cellulose.

QUESTIONS

www.thereliefproducts.com, 1-888-969-6855

Indications and usage

Uses:*

According to homeopathic indications these ingredients temporarily relieve symptoms such as: • loose stools • bloating • dry, hard stools • cramping • irritability • flatulence • irregularity • stomach discomfort after a diagnosis by a physician.

*These statements are based upon traditional homeopathic practice. They have not been reviewed by the Food and Drug Administration.

Stop use

Stop use and ask a doctor if:

- You experience worsening symptoms.
- If symptoms last longer than 7 days.